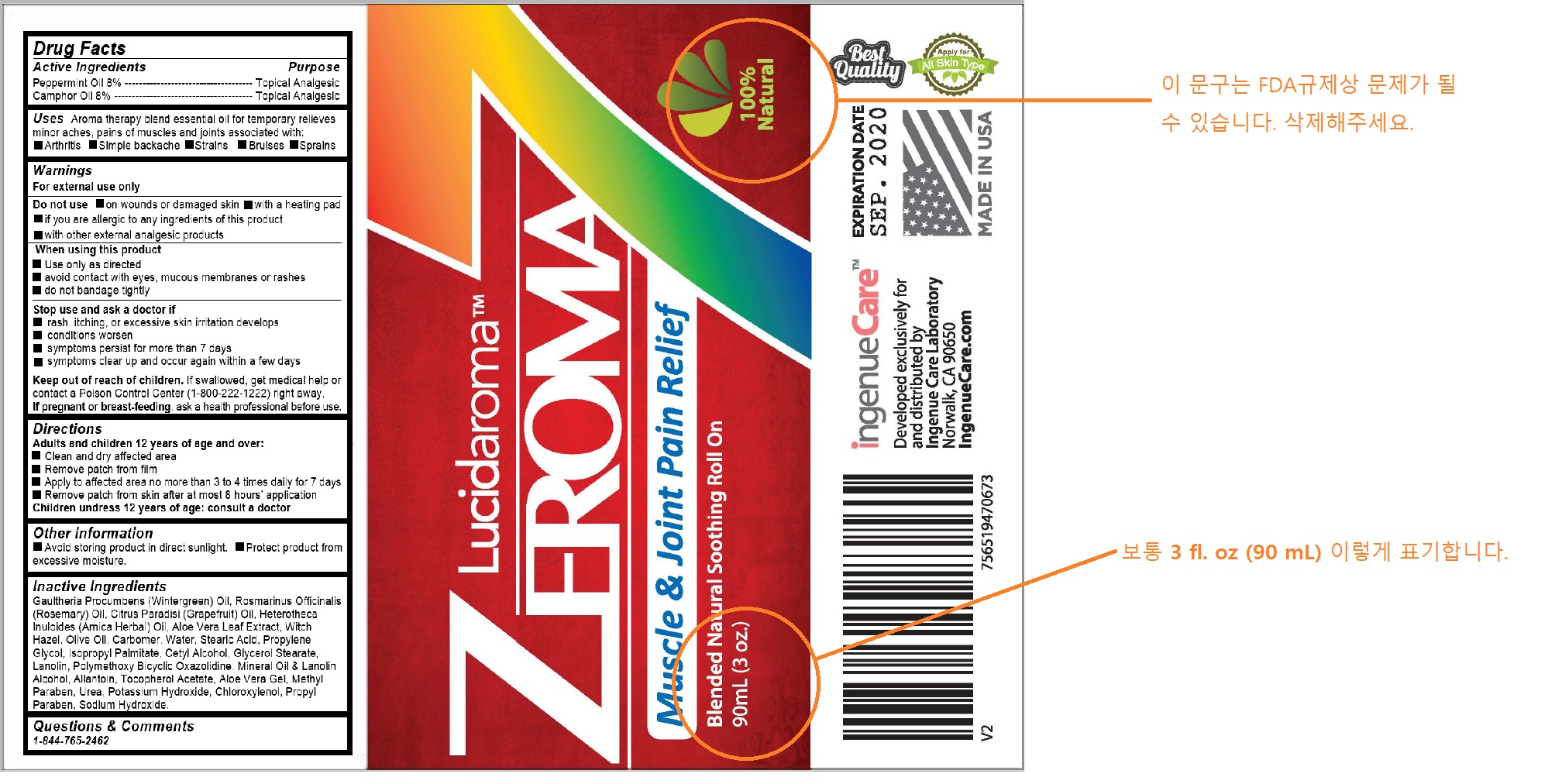 DRUG LABEL: Zeroma7
NDC: 72589-100 | Form: GEL
Manufacturer: Ingenue Care Inc
Category: otc | Type: HUMAN OTC DRUG LABEL
Date: 20181008

ACTIVE INGREDIENTS: CAMPHOR (SYNTHETIC) 6.8 g/85 g; PEPPERMINT OIL 6.8 g/85 g
INACTIVE INGREDIENTS: GAULTHERIA PROCUMBENS LEAF

Zeroma7

Uses

Uses Aroma therapy blend essential oil for temporary relieves minor aches, pains of muscles and joints associated with:

Arthritis Simple backache Strains Bruises Sprains

Warnings

For external use only

Do not use on wounds or damaged skin with a heating pad

if you are allergic to any ingredients of this product

with other external analgesic products

When using this product

Use only as directed

avoid contact with eyes, mucous membranes or rashes

do not bandage tightly

Stop use and ask a doctor if

rash, itching, or excessive skin irritation develops

conditions worsen

symptoms persist for more than 7 days

symptoms clear up and occur again within a few days

Keep out of reach of children

If swallowed, get medical help or contact a Poison Control Center (1-800-222-1222) right away.

If pregnant or breast-feeding, ask a health professional before use

Active Ingredients

Peppermint Oil 8% ------------------------------------ Topical Analgesic

Camphor Oil 8% --------------------------------------- Topical Analgesic

Purpose

Topical Analgesic

Directions

Adults and children 12 years of age and over:

Clean and dry affected area

Remove patch from film

Apply to affected area no more than 3 to 4 times daily for 7 days

Remove patch from skin after at most 8 hours’ application

Children undress 12 years of age: consult a doctor

Inactive Ingredients

Gaultheria Procumbens (Wintergreen) Oil, Rosmarinus Officinalis (Rosemary) Oil, Citrus Paradisi (Grapefruit) Oil, Heterotheca Inuloides (Arnica Herbal) Oil, Aloe Vera Leaf Extract, Witch Hazel, Olive Oil, Carbomer, Water, Stearic Acid, Propylene Glycol, Isopropyl Palmitate, Cetyl Alcohol, Glycerol Stearate, Lanolin, Polymethoxy Bicyclic Oxazolidine, Mineral Oil & Lanolin Alcohol, Allantoin, Tocopherol Acetate, Aloe Vera Gel, Methyl Paraben, Urea, Potassium Hydroxide, Chloroxylenol, Propyl Paraben, Sodium Hydroxide.